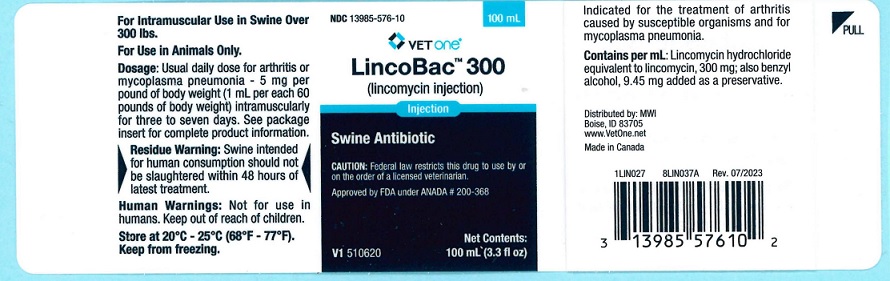 DRUG LABEL: LincoBac 300
NDC: 13985-576 | Form: INJECTION
Manufacturer: MWI/VetOne
Category: animal | Type: PRESCRIPTION ANIMAL DRUG LABEL
Date: 20240401

ACTIVE INGREDIENTS: LINCOMYCIN HYDROCHLORIDE 300 mg/1 mL
INACTIVE INGREDIENTS: BENZYL ALCOHOL 9.45 mg/1 mL

DESCRIPTION

LincoBac™ 300

(lincomycin injection)

For use in swine weighing 300 pounds or more.

For Intramuscular Use in Swine Only

CAUTION: Federal law restricts this drug to use by or on the order of a licensed veterinarian.

LincoBac 300 contains lincomycin hydrochloride, an antibiotic produced by Streptomyces lincolnensis var. lincolnensis which is chemically distinct from all other clinically available antibiotics and is isolated as a white crystalline solid.

ADVERSE REACTIONS

ADVERSE REACTIONS: The intramuscular administration to swine may cause a transient diarrhea or loose stools. Although this effect has rarely been reported, one must be alert to the possibility that it may occur. Should this occur, it is important that the necessary steps be taken to prevent the effects of dehydration.

The Safety Data Sheet (SDS) contains more detailed occupational safety information. To report adverse drug events, for technical assistance or to obtain a copy of the SDS, contact Bimeda, Inc. at 1-888-524-6322. For additional information about adverse drug experience reporting for animal drugs, contact FDA at 1-888-FDA-VETS or online at www.fda.gov/reportanimalae.

DOSAGE AND ADMINISTRATION: For arthritis or mycoplasma pneumonia – 5 mg per pound of body weight intramuscularly once daily for three to seven days as needed. One mL per 60 lb body weight will provide 5 mg/lb.
For optimal results, initiate treatment as soon as possible.

As with any multi-dose vial, practice aseptic techniques in withdrawing each dose. Adequately clean and disinfect the vial closure prior to entry with a sterile needle and syringe. No vial closure should be entered more than 20 times.

HOW SUPPLIED

Each mL contains: Lincomycin hydrochloride equivalent to lincomycin 300 mg; also benzyl alcohol 9.45 mg added as preservative.

HOW SUPPLIED: LincoBac 300, 300 mg/mL: For use in swine weighing 300 pounds or more. Supplied in 100 mL multiple dose vial.

INDICATIONS FOR SWINE:

LincoBac 300 is indicated for the treatment of infectious forms of arthritis caused by organisms sensitive to its activity. This includes most of the organisms responsible for the various infectious arthritides in swine, such as staphylococci, streptococci, Erysipelothrix and Mycoplasma spp.

It is also indicated for the treatment of mycoplasma pneumonia.

STORAGE AND HANDLING

Store at 20°-25°C (68°-77°F). Keep from freezing.

CONTRAINDICATIONS

CONTRAINDICATIONS: As with all drugs, the use of LincoBac 300 is contraindicated in animals previously found to be hypersensitive to the drug.

WARNINGS

Residue Warning: Swine intended for human consumption should not be slaughtered within 48 hours of latest treatment.

Human Warnings: Not for use in humans. Keep out of reach of children.

CAUTION: If no improvement is noted within 48 hours, consult a veterinarian.